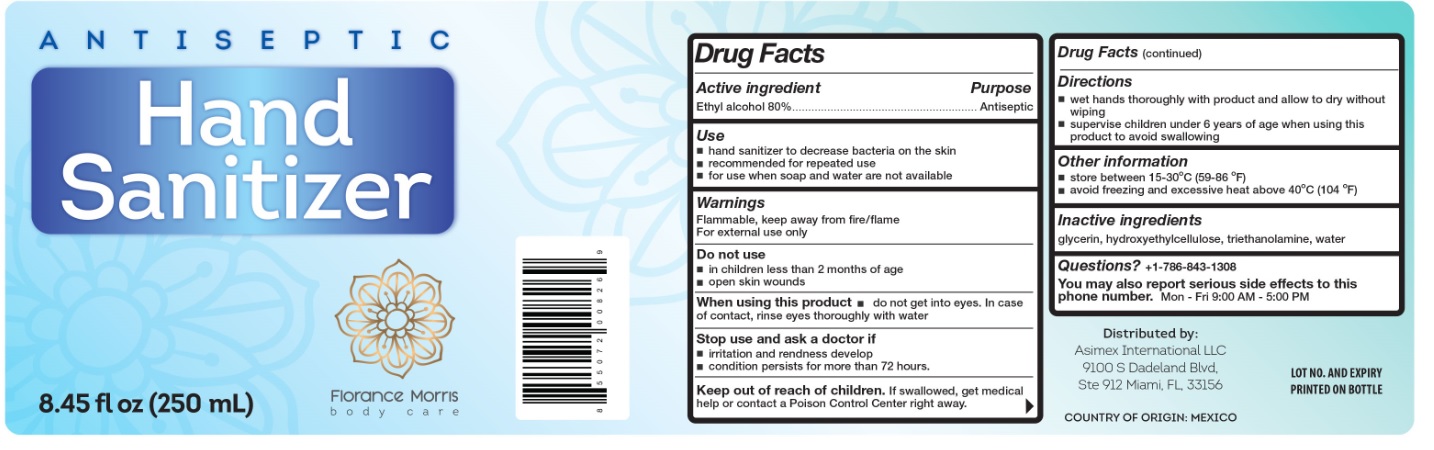 DRUG LABEL: Florance Morris Antiseptic Hand Sanitizer
NDC: 76612-180 | Form: GEL
Manufacturer: Asimex International Llc
Category: otc | Type: HUMAN OTC DRUG LABEL
Date: 20200504

ACTIVE INGREDIENTS: ALCOHOL 80 mL/100 mL
INACTIVE INGREDIENTS: GLYCERIN; HYDROXYETHYL CELLULOSE, UNSPECIFIED; TROLAMINE; WATER

Florance Morris body care ANTISPETIC HAND SANTITIZER

Active ingredient

Ethyl alcohol 80%

Purpose

Antiseptic

Use

■To decrease bacteria on the skin that could cause disease

■Recommended for repeated use

Warnings

For external use only: hands.

■Flammable ■Keep away from fire or flame

When using this product ■Keep out of eyes ■In case of contact with eyes, flush thoroughly with water ■Avoid contact with broken skin ■Do not inhale or ingest

Stop use and ask a doctor if ■Irritation or redness develops. ■Condition persists for more than 72 hours

Keep out of reach of children. If swallowed, get medical help or contact a Poison Control Center right away

Directions

Thoroughly cover your hands with product and allow to dry without wiping ■Children under 6 years of age should be supervised when using this product ■Not recommended for infants

Other information

Store below 105°F ■May discolor some fabrics ■Harmful to wood finishes and plastics

Inactive ingredients

Cellulosic thickener, Glycerin, Triethanolamine, Water

Questions? +1-786-843-1308
You may also report serious side effects to this phone number.
Mon-Fri 9:00 AM - 5:00 PM

Florance Morris

body care

Distributed by: Asimex International LLC

9100 S Dadeland Blvd,

Ste 912 Miami, FL, 33156

COUNTRY OF ORIGIN: MEXICO

Lot No:

Expiry: